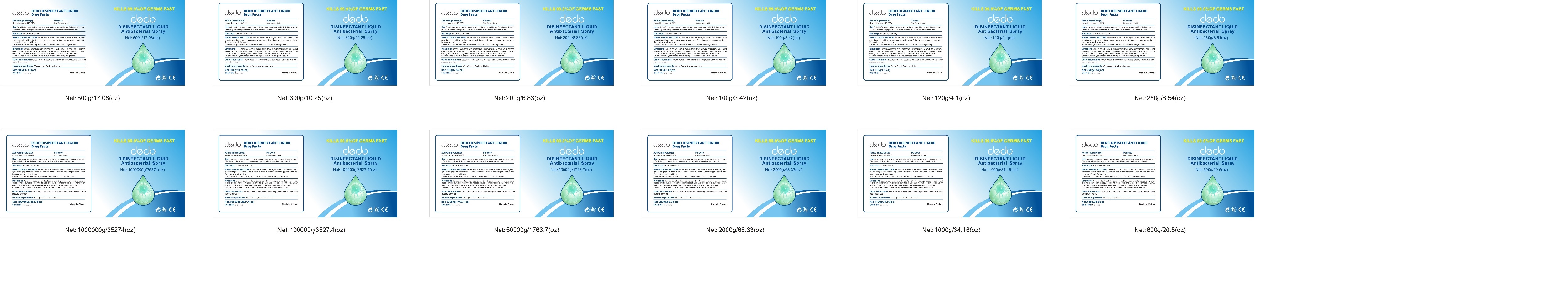 DRUG LABEL: Disinfectant liquid Antibacterial
NDC: 74534-014 | Form: SPRAY
Manufacturer: Guangzhou Dedo Pharmaceutical Co.,Ltd
Category: otc | Type: HUMAN OTC DRUG LABEL
Date: 20200424

ACTIVE INGREDIENTS: HYPOCHLOROUS ACID 0.02 g/100 g
INACTIVE INGREDIENTS: SODIUM CHLORIDE; WATER

Active Ingredient(s)

HYPOCHLOROUS ACID 0.02%

Purpose

DISINFECTANT LIQUID

Use

SUITABLE FOR GENERAL OBJECT SURFACE,SKIN SURFACE,VEGETABLE AND FRUIT DISINFECTION ETC.EFFECTIVELY INHIBIT STAPHYLOCOCCUS AUREUS,CANDIDA ALBICANS AND ESCHERICHIA COLI.

Warnings

for external use only.

do not use in or near the eyes.In case of contact.rinse eyes thoroughly with water.Stop use and ask doctor if irritation or rash appears and lasts.

Keep out of teach for children.

If swallowed,get medical help or contact a Poison Control Center right away.

Directions

GENERAL OBJECT AND SKIN DISINFECTION:DIRECT SPRAYING OF PRODUCTS ON GENERAL OBJECTS OR SKIN SURFACES REQUIRING DISINFECTION;FRUITS AND VEGETABLES DISINFECTION:SPRAY DIRECTLY ON THE FRUIT AND VEGETABLE SURFACE AND FINSE WITH WATER AFTER 10 MINUTES

Children under 6 years of age should be supervised when using this product.

Other information

Please keep it in a cool and ventilated place.DO NOT MIX WITH OTHER PRODUCTS OR WATER.

Inactive ingredients

Water(Aqua),SODIUM CHLORIDE